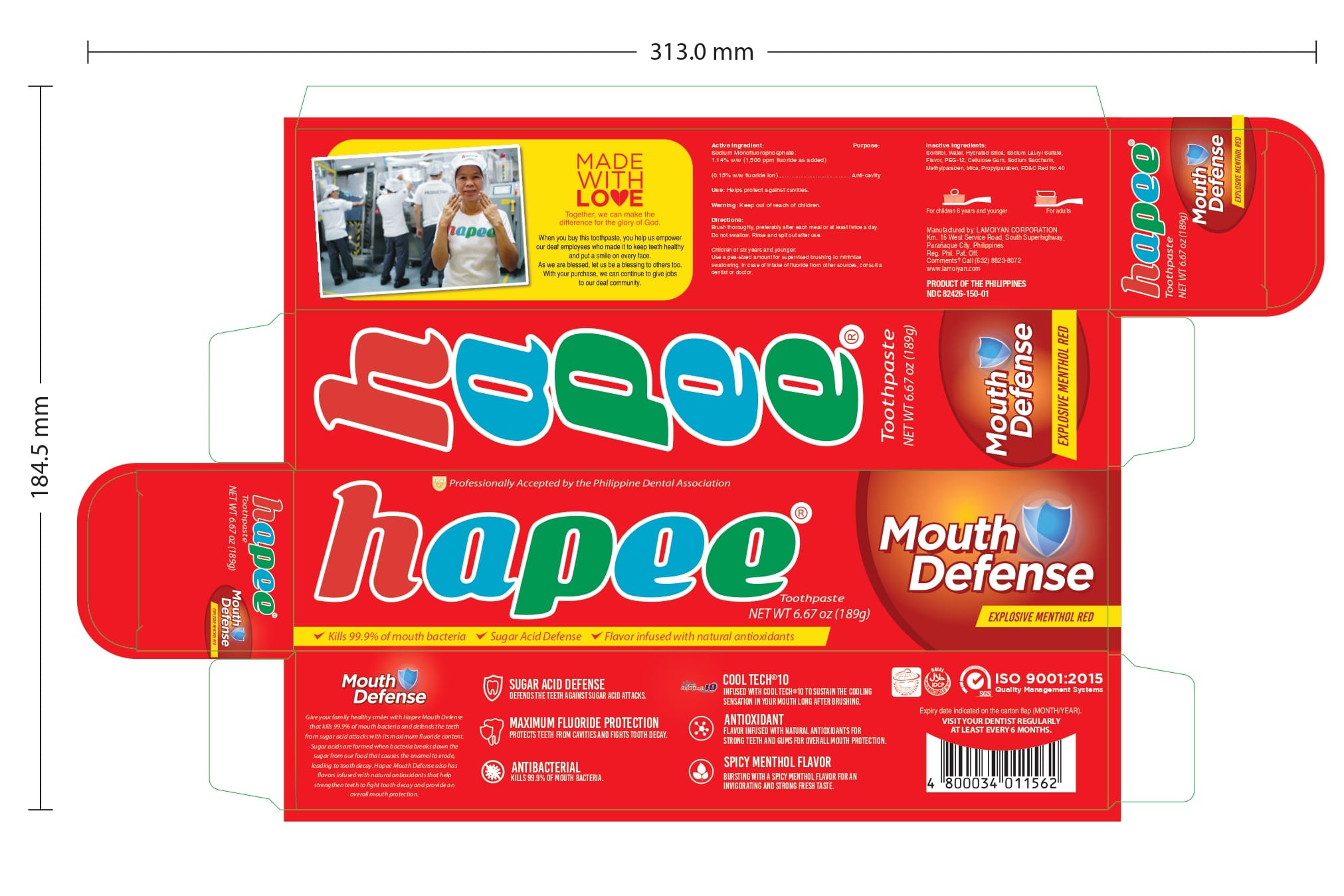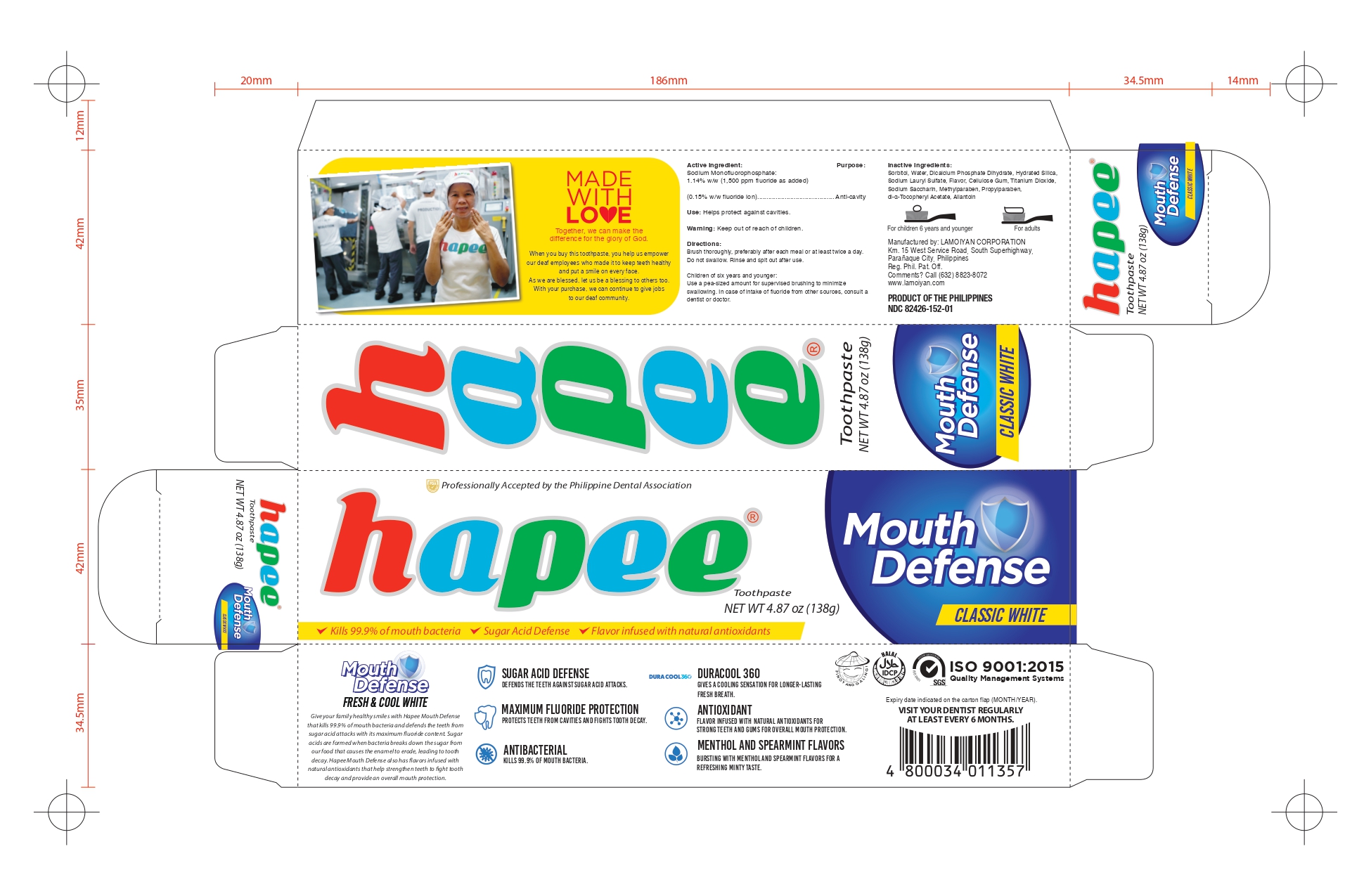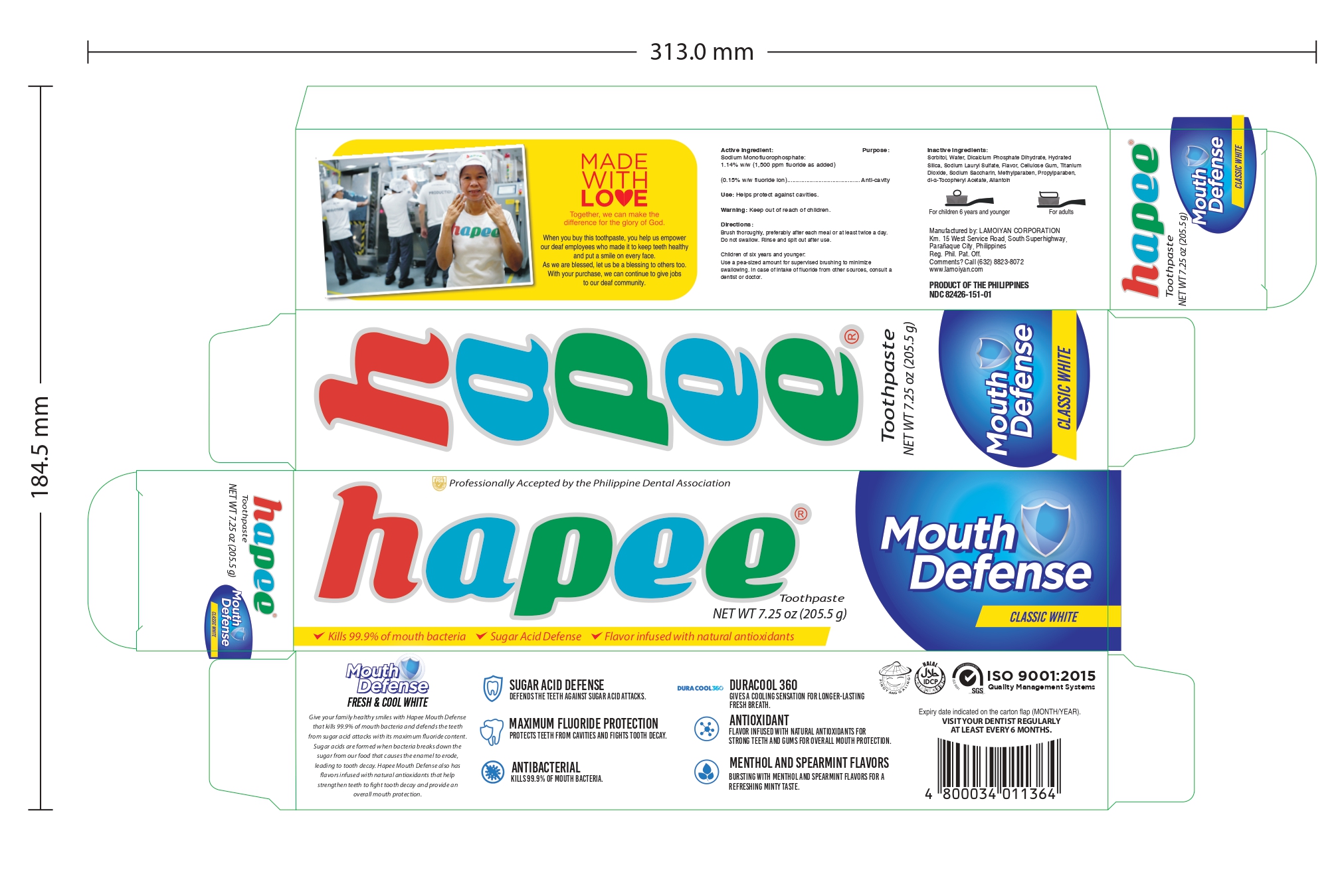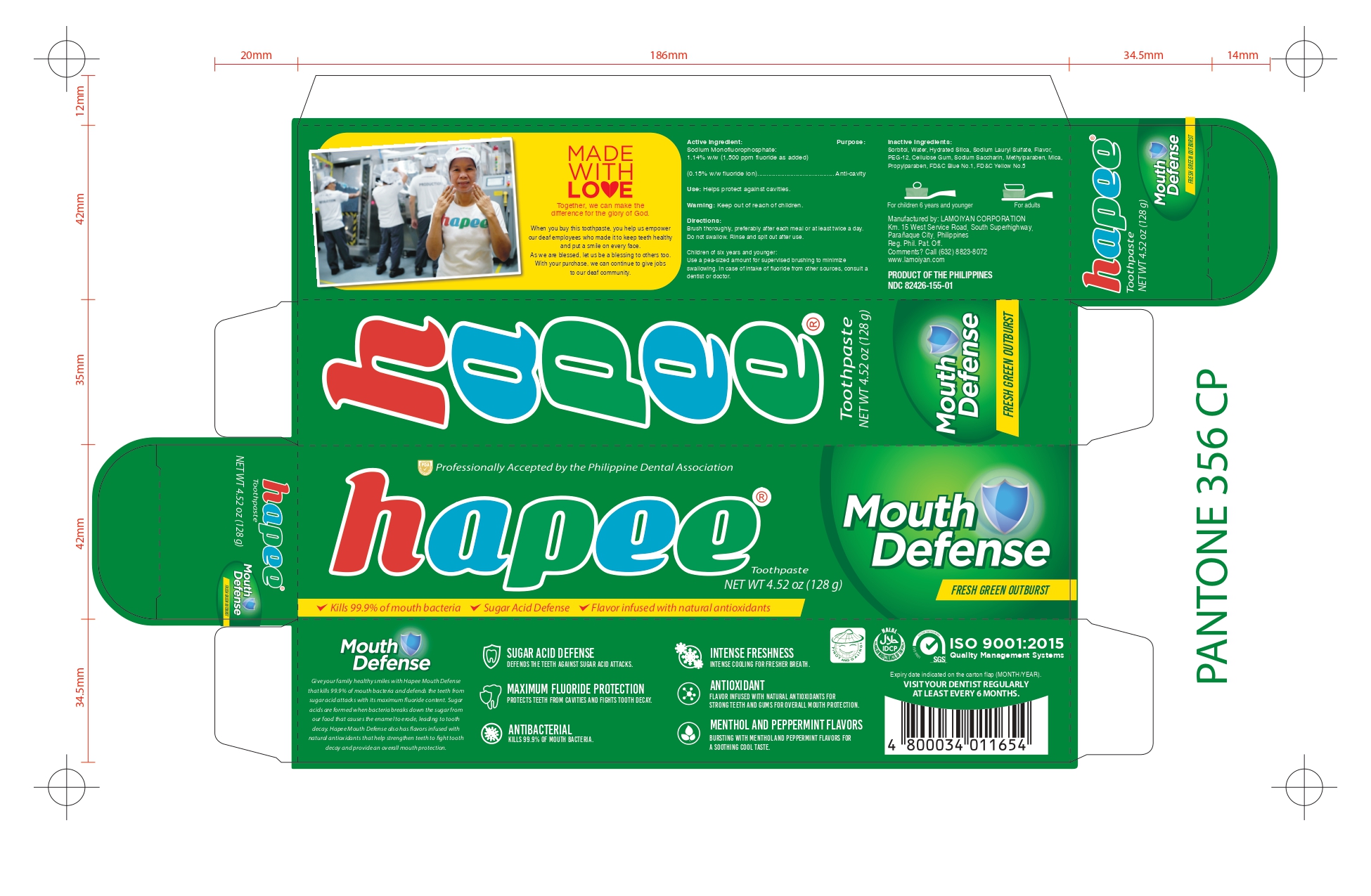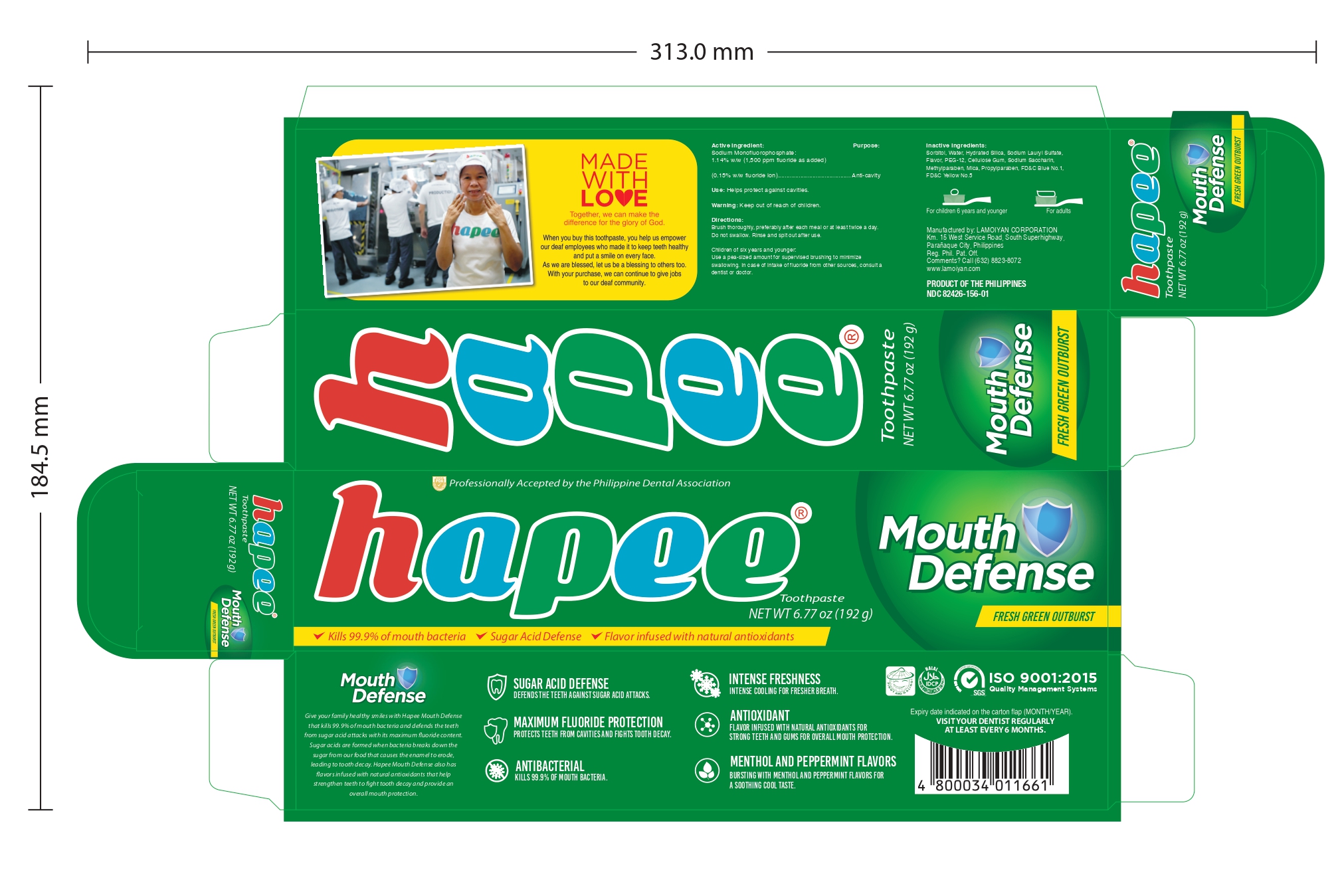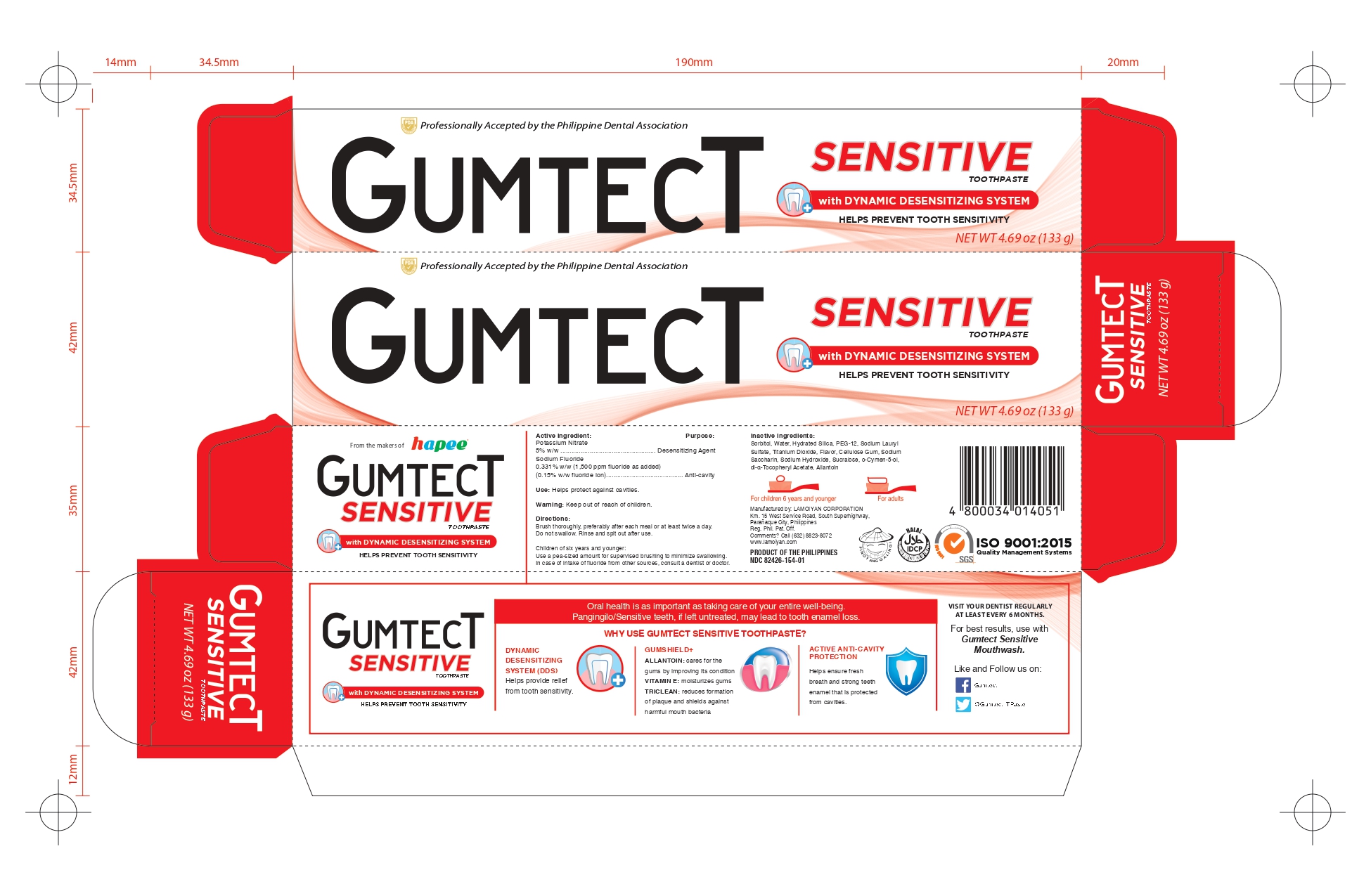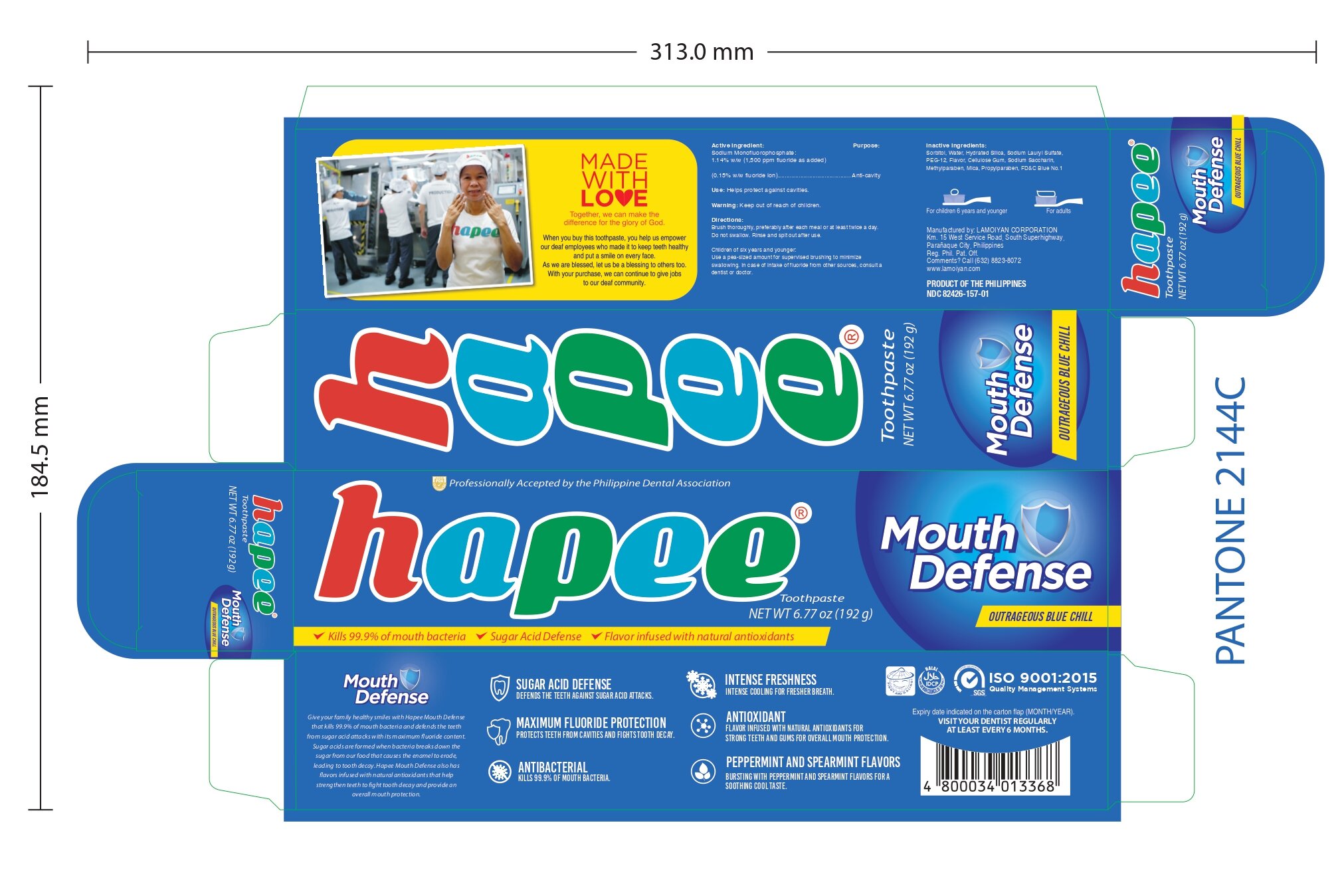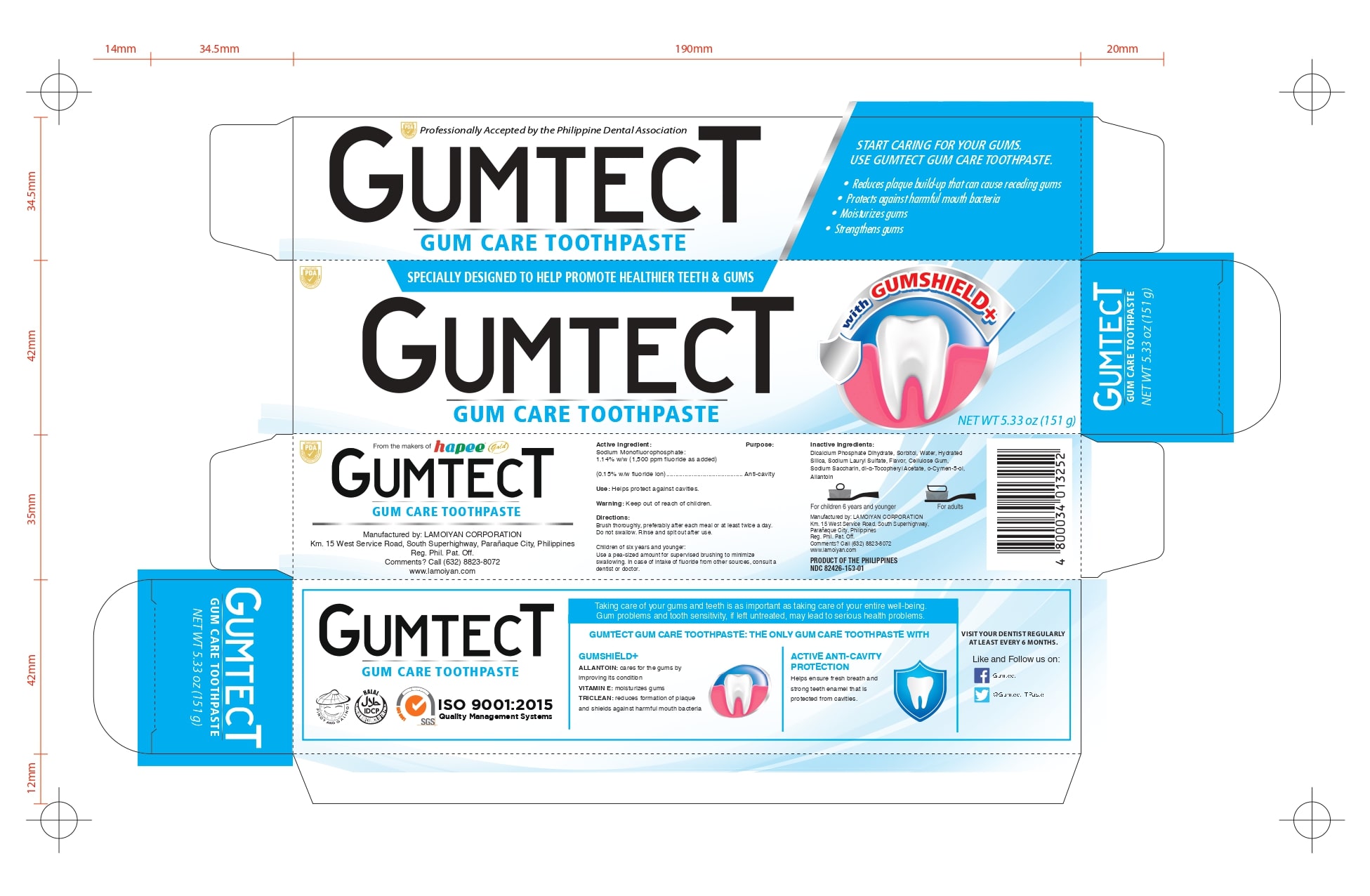 DRUG LABEL: HAPEE FRESH AND COOL WHITE 150
NDC: 82426-151 | Form: GEL, DENTIFRICE
Manufacturer: LAMOIYAN CORPORATION
Category: otc | Type: HUMAN OTC DRUG LABEL
Date: 20260205

ACTIVE INGREDIENTS: SODIUM MONOFLUOROPHOSPHATE 0.15 g/100 g
INACTIVE INGREDIENTS: POLYETHYLENE GLYCOL 600; CARYOPHYLLENE; ISOMENTHONE, (+)-; .BETA.-PINENE; MYRCENE; MENTHOL; CARVONE; EUGENOL; .ALPHA.-PINENE; SORBITOL; WATER; HYDRATED SILICA; SODIUM LAURYL SULFATE; CARBOXYMETHYLCELLULOSE; TITANIUM DIOXIDE; SACCHARIN SODIUM; METHYLPARABEN; PROPYLPARABEN; ALPHA-TOCOPHEROL ACETATE; ALLANTOIN; LIMONENE, (-)-; CINEOLE; ANETHOLE; MENTHONE; LIMONENE, (+)-

WARNINGS AND PRECAUTIONS SECTION

Children of six years and younger: Use a pea-sized amount for supervised brushing to minimize swallowing. In case of intake of fluoride from other sources, consult a dentist or doctor.

Direction

Brush thoroughly, preferably after each meal or at least twice a day. Do not swallow. Rinse and spit out after use.

Warning

Keep out of reach of children

Inactive Ingredients

Sorbitol, Water, Hydrated Silica, Sodium Lauryl Sulfate, Flavor, PEG-12, Cellulose Gum, Sodium Saccharin, Methylparaben, Mica, Propylparaben, FD&C Red No.40

Active Ingredient

Sodium Monofluorophosphate:
1.14% w/w (1,500 ppm fluoride as added)
(0.15% w/w fluoride ion)

Use

Helps protect against cavities

PURPOSE

Anti-cavity